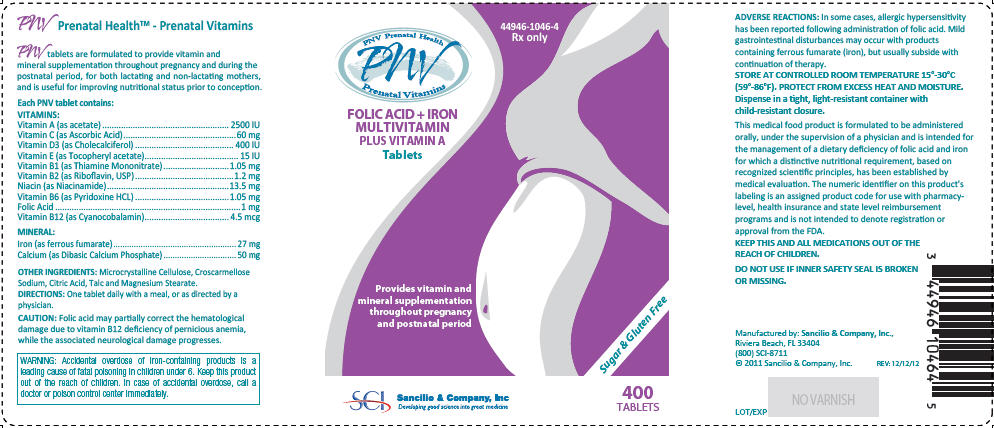 DRUG LABEL: PNV Prenatal Vitamin
NDC: 44946-1046 | Form: TABLET
Manufacturer: Sancilio & Company Inc
Category: prescription | Type: HUMAN PRESCRIPTION DRUG LABEL
Date: 20121214

ACTIVE INGREDIENTS: .Alpha.-Tocopherol Acetate, DL- 15 [iU]/1 1; Ascorbic Acid 60 mg/1 1; Cholecalciferol 400 [iU]/1 1; Cyanocobalamin 4.5 ug/1 1; Folic Acid 1 mg/1 1; Ferrous fumarate 27 mg/1 1; Calcium Phosphate, Dibasic, Anhydrous 50 mg/1 1; Niacinamide 13.5 mg/1 1; Pyridoxine Hydrochloride 1.05 mg/1 1; Riboflavin 1.2 mg/1 1; Thiamine Mononitrate 1.05 mg/1 1; Vitamin A Acetate 2500 [iU]/1 1
INACTIVE INGREDIENTS: Cellulose, Microcrystalline; Croscarmellose sodium; Anhydrous Citric Acid; Talc; Magnesium stearate

PNV Prenatal Health™ - Prenatal Vitamins

PNV tablets are formulated to provide vitamin and mineral supplementation throughout pregnancy and during the postnatal period, for both lactating and non-lactating mothers, and is useful for improving nutritional status prior to conception.

DESCRIPTION

Each PNV tablet contains:

VITAMINS:
Vitamin A (as acetate) | 2500 IU
Vitamin C (as Ascorbic Acid) | 60 mg
Vitamin D3 (as Cholecalciferol) | 400 IU
Vitamin E (as Tocopheryl acetate) | 15 IU
Vitamin B1 (as Thiamine Mononitrate) | 1.05 mg
Vitamin B2 (as Riboflavin, USP) | 1.2 mg
Niacin (as Niacinamide) | 13.5 mg
Vitamin B6 (as Pyridoxine HCL) | 1.05 mg
Folic Acid | 1 mg
Vitamin B12 (as Cyanocobalamin) | 4.5 mcg
MINERAL:
Iron (as ferrous fumarate) | 27 mg
Calcium (as Dibasic Calcium Phosphate) | 50 mg

OTHER INGREDIENTS

Microcrystalline Cellulose, Croscarmellose Sodium, Citric Acid, Talc and Magnesium Stearate.

DIRECTIONS

One tablet daily with a meal, or as directed by a physician.

CAUTION

Folic acid may partially correct the hematological damage due to vitamin B12 deficiency of pernicious anemia, while the associated neurological damage progresses.

WARNING

Accidental overdose of iron-containing products is a leading cause of fatal poisoning in children under 6. Keep this product out of the reach of children. In case of accidental overdose, call a doctor or poison control center immediately.

ADVERSE REACTIONS

In some cases, allergic hypersensitivity has been reported following administration of folic acid. Mild gastrointestinal disturbances may occur with products containing ferrous fumarate (iron), but usually subside with continuation of therapy.

HOW SUPPLIED

STORAGE AND HANDLING

STORE AT CONTROLLED ROOM TEMPERATURE 15°-30°C (59°-86°F). PROTECT FROM EXCESS HEAT AND MOISTURE. Dispense in a tight, light-resistant container with child-resistant closure.

This medical food product is formulated to be administered orally, under the supervision of a physician and is intended for the management of a dietary deficiency of folic acid and iron for which a distinctive nutritional requirement, based on recognized scientific principles, has been established by medical evaluation. The numeric identifier on this product's labeling is an assigned product code for use with pharmacy-level, health insurance and state level reimbursement programs and is not intended to denote registration or approval from the FDA.

KEEP THIS AND ALL MEDICATIONS OUT OF THE REACH OF CHILDREN.

DO NOT USE IF INNER SAFETY SEAL IS BROKEN OR MISSING.

Manufactured by: Sancilio & Company, Inc.,
Riviera Beach, FL 33404
(800) SCI-8711

© 2011 Sancilio & Company, Inc.

REV: 12/07/12

PRINCIPAL DISPLAY PANEL - 400 Tablet Bottle Label

44946-1046-4
Rx only

PNV Prenatal Health
PNV
Prenatal Vitamins

FOLIC ACID + IRON
MULTIVITAMIN
PLUS VITAMIN A
Tablets

Provides vitamin and
mineral supplementation
throughout pregnancy
and postnatal period

Sugar & Gluten Free

SCI
Sancilio & Company, Inc
Developing good science into great medicine

400
TABLETS